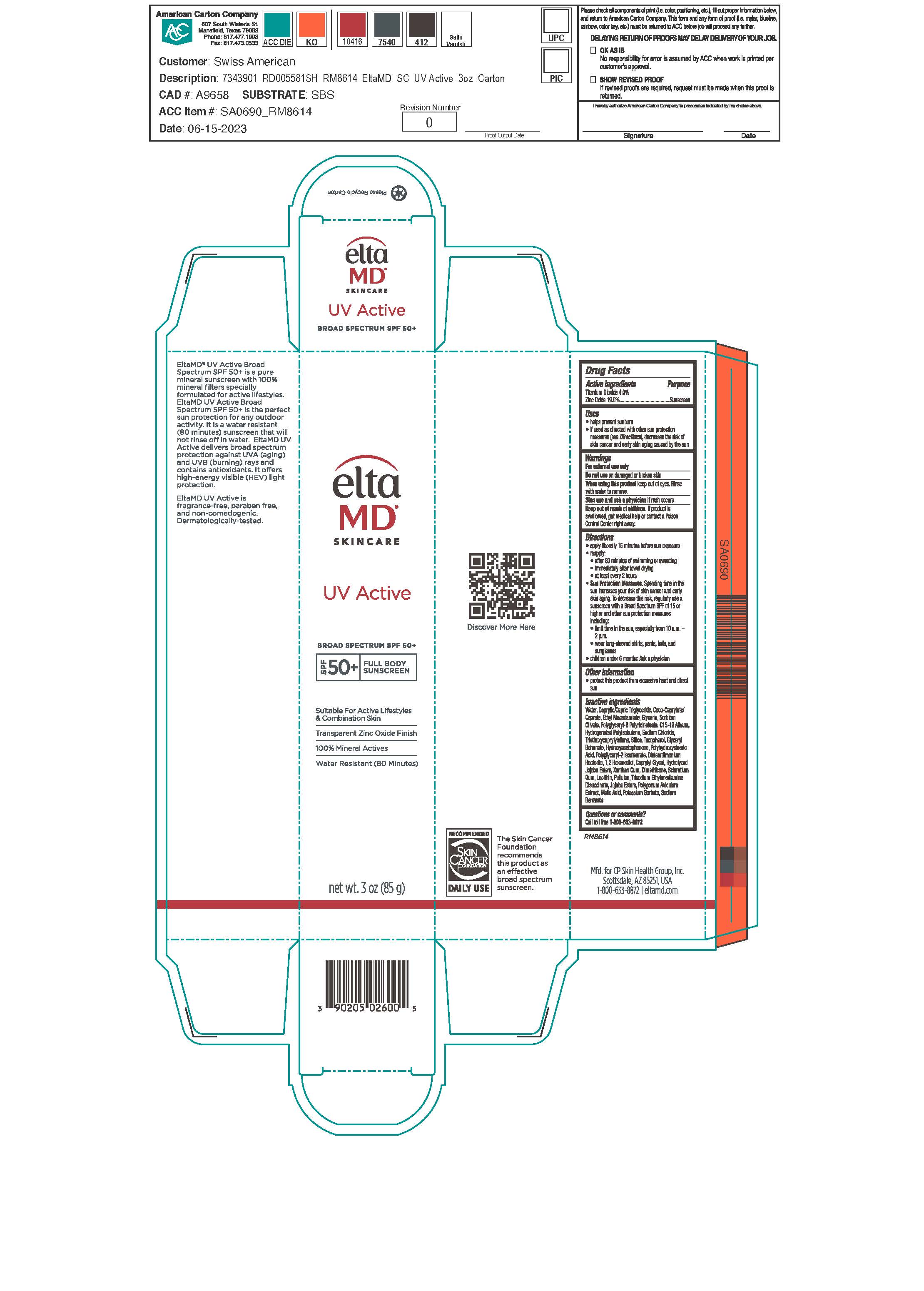 DRUG LABEL: EltaMD UV Active
NDC: 72043-2600 | Form: CREAM
Manufacturer: CP Skin Health Group, Inc.
Category: otc | Type: HUMAN OTC DRUG LABEL
Date: 20231109

ACTIVE INGREDIENTS: ZINC OXIDE 190 g/1000 g; TITANIUM DIOXIDE 40 g/1000 g
INACTIVE INGREDIENTS: WATER; SODIUM CHLORIDE; XANTHAN GUM; LECITHIN, SOYBEAN; PULLULAN; ALUMINUM SILICATE; TRISODIUM ETHYLENEDIAMINE DISUCCINATE; HYDROXYACETOPHENONE; glycerin; ETHYL MACADAMIATE; TOCOPHEROL; MALIC ACID; POLYHYDROXYSTEARIC ACID (2300 MW); TRIETHOXYCAPRYLYLSILANE; C15-19 ALKANE; DIMETHICONE; SORBITAN OLIVATE; .ALPHA.-TOCOPHEROL, DL-; ETHYLHEXYLGLYCERYL BEHENATE; DISTEARDIMONIUM HECTORITE; POLYGLYCERYL-2 ISOSTEARATE; BETASIZOFIRAN; 1,2-HEXANEDIOL; CAPRYLYL GLYCOL; HYDROLYZED JOJOBA ESTERS (ACID FORM); MEDIUM-CHAIN TRIGLYCERIDES; COCO-CAPRYLATE/CAPRATE; HYDROGENATED POLYBUTENE (1300 MW); POLYGONUM AVICULARE TOP

EltaMD UV Active

Warnings

For external use only. Do not use on damaged or broken skin. Stop use and ask physician if rash occurs. When using this product keep out of eyes. Rinse with water to remove. If product is swallowed, get medical help or contact a Poison Control Center right away.

Keep out of reach of children.

Active Ingredients

Zinc Oxide 19.0% Sunscreen

Titanium Dioxide 4.0% Sunscreen

Directions

Apply liberally 15 minutes before sun exposure. Reapply after 80 minutes of swimming or sweating, immediately after towel drying, at least every two hours. Sun protection measures: Spending time in the sun increases your risk of skin cancer and early skin aging. To decrease this risk, regularly use sunscreen with a broad-spectrum SPF value of 15 or higher. Limit time in the sun, especially from 10 am to 2 pm. Wear long sleeved shirts, pants, hats and sunglasses. Before use on children under 6 months, ask a physician.

Questions

Questions or Comments?

1-800-633-8872

Other information

Protect this product from excessive heat and direct sun.

Inactive ingredients

water, caprylic/capric trigylceride, coco-caprylate/caprate, ethyl macadamiate, glycerin, sorbitan olivate, polyglyceryl-6 polyricinoleate, C15-19 alkane, hydrogenated polyisobutene, sodium chloride, triethoxycaprylylsilane, silica, glyceryl beheanate, hydroxyacetophenone, polyglyceryl-2 isostearate, polyhydroxysearic acid, disteardimonium hectorite, 1,2-hexanediol, caprylyl glycol, hydrolyzed jojoba esters, xanthan gum, diemthicone, sclerotium gum, trisodium ethylenediamine disuccinate, lecithin, pullulan, jojoba esters, polygonum aviculare extract, tocopherol, malic acid